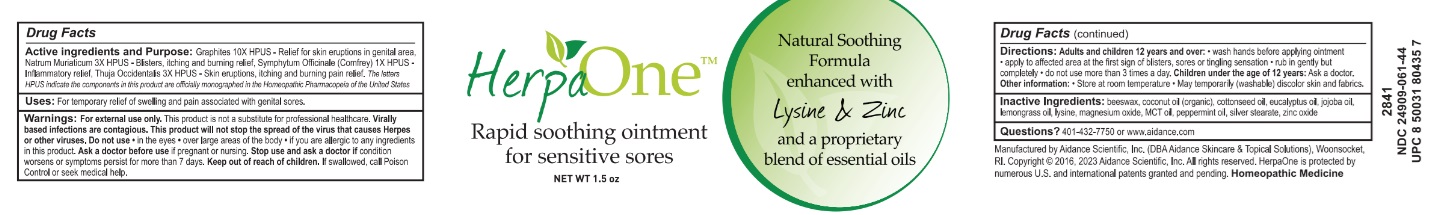 DRUG LABEL: HerpaOne
NDC: 24909-061 | Form: OINTMENT
Manufacturer: Aidance Scientific, Inc, DBA Aidance Skincare & Topical Solutions
Category: homeopathic | Type: HUMAN OTC DRUG LABEL
Date: 20250711

ACTIVE INGREDIENTS: GRAPHITE 10 [hp_X]/1 g; SODIUM CHLORIDE 3 [hp_X]/1 g; SYMPHYTUM OFFICINALE WHOLE 1 [hp_X]/1 g; THUJA OCCIDENTALIS LEAFY TWIG 3 [hp_X]/1 g
INACTIVE INGREDIENTS: COTTONSEED OIL; EUCALYPTUS OIL; JOJOBA OIL; WEST INDIAN LEMONGRASS OIL; LYSINE; MAGNESIUM OXIDE; PALM OIL; PEPPERMINT OIL; SILVER STEARATE; ZINC OXIDE; YELLOW WAX; COCONUT OIL

D24909-061 HerpaOne

Active Ingredient Purpose

Graphites 10X HPUS ..................................................Relief for skin eruptions in genital area
Natrum Muriaticum 3X HPUS .......................................Blisters, itching and burning relief
Symphytum Officinale (Comfrey) 1X HPUS.....................Inflammatory relief
Thuja Occidentalis 3X HPUS ........................................Skin eruptions, itching and burning pain relief

The letters HPUS indicate the components in this product are officially monographed in the Homeopathic Pharmacopeia of the United States.

Uses

For temporary relief of swelling and pain associated with genital sores.

Warnings

For external use only.
This product is not a substitute for professional healthcare. Virally based infections are contagious. This product will not stop the spread of the virus that causes Herpes or other viruses. Do not use• in the eyes • over large areas of the body • if you are allergic to any ingredients in this product. Ask a doctor before useif pregnant or nursing. Stop use and ask a doctor ifcondition worsens or symptoms persist for more than 7 days. Keep out of reach of children. If swallowed, call Poison Control or seek medical help.

Directions

Adults and children 12 years and over: • wash hands before applying ointment
• apply to affected area at the first sign of blisters, sores or tingling sensation • rub in gently but completely • do not use more than 3 times a day.

Children under the age of 12 years: Ask a doctor

Inactive Ingredients

beeswax, coconut oil (organic), cottonseed oil, eucalyptus oil, jojoba oil, lemongrass oil, lysine, magnesium oxide, MCT oil, peppermint oil, silver stearate, zinc oxide

Other information

Store at room temperature. May temporarily (washable) discolor skin and fabrics.